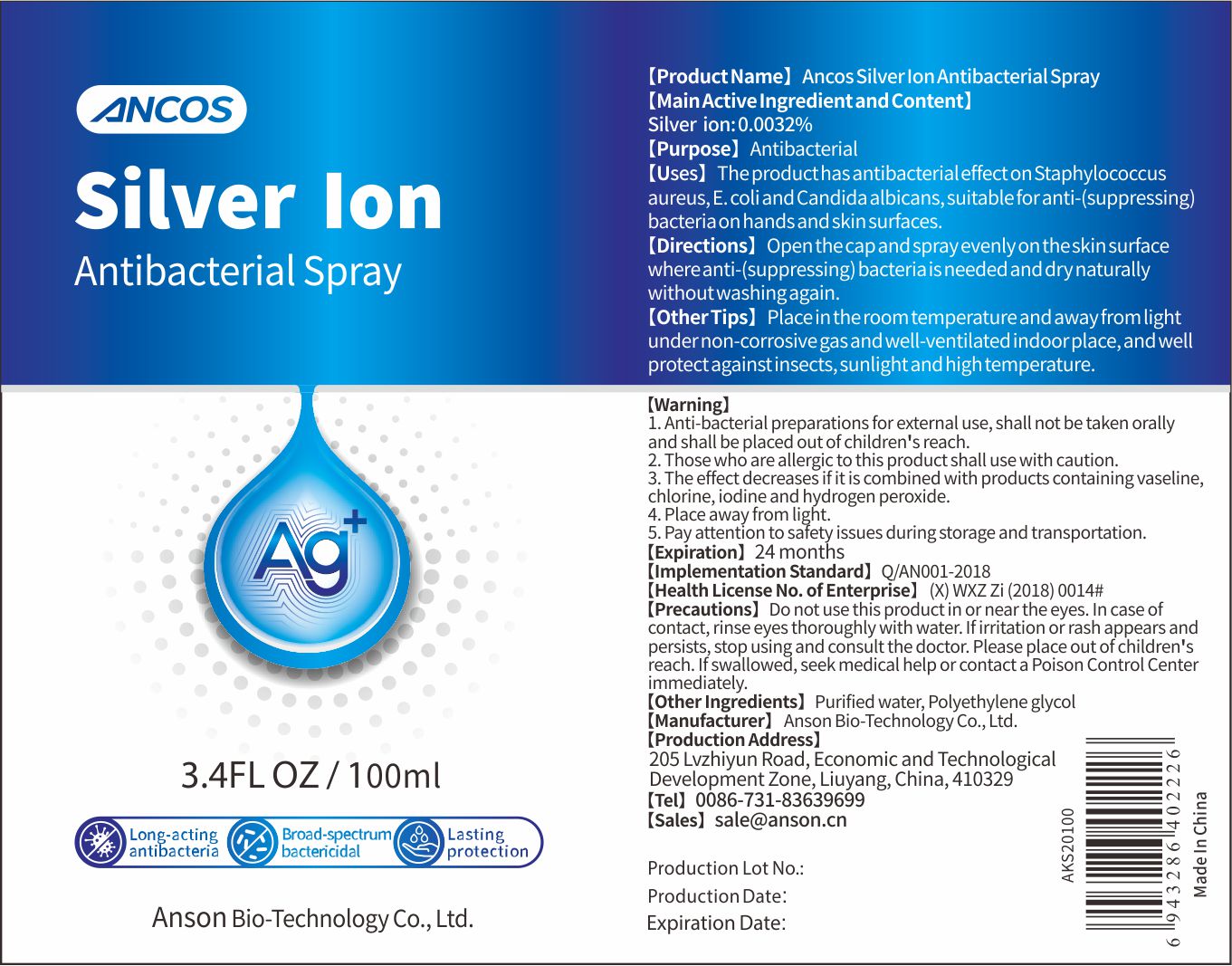 DRUG LABEL: Ancos Silver Ion Antibacterial
NDC: 75139-005 | Form: LIQUID
Manufacturer: Anson Bio-Technology Co., Ltd.
Category: otc | Type: HUMAN OTC DRUG LABEL
Date: 20200427

ACTIVE INGREDIENTS: SILVER CATION 0.0032 g/100 mL
INACTIVE INGREDIENTS: POLYETHYLENE GLYCOL, UNSPECIFIED; WATER

Silver Ion Anti-bacterial Spray

Main Active Ingredient and Content

Silver ion: 0.0032%

Purpose

Antibacterial

Uses

The product has antibacterial effect on Staphylococcus aureus, E. coli and Candida albicans, suitable for anti-(suppressing)bacteria on hand sand skin surfaces

Directions

Open cap and spray on the skin surface where anti-(suppressing)bacteria is needed and dry naturally without washing again

Other Tips

Place in the room temperature and away from light under non-corrosive gas and well-ventilated indoor place, and well protect against insects, sunlight and high temperature

Warning

- Anti-bacterial preparations for external use, shall not be taken orally and shall be placed out of children's reach
- Those who are allergic to this product shall use with caution
- The effect decreases if it is combined with products containing vaseline, chlorine, iodine and hydrogen peroxide.,
- Place away from light
- Pay attention to safety issues during storage and transportation

Precautions

Do not use this product in or near the eyes. In case of contact, rinse eyes thoroughly with water. If irritation or rash appears and persists, stop using and consult the doctor. Please place out of children's reach If swallowed, seek medical help or contact a Poison Control Center immediately.

Other Ingredients

Purified water, Polyethylene glycol